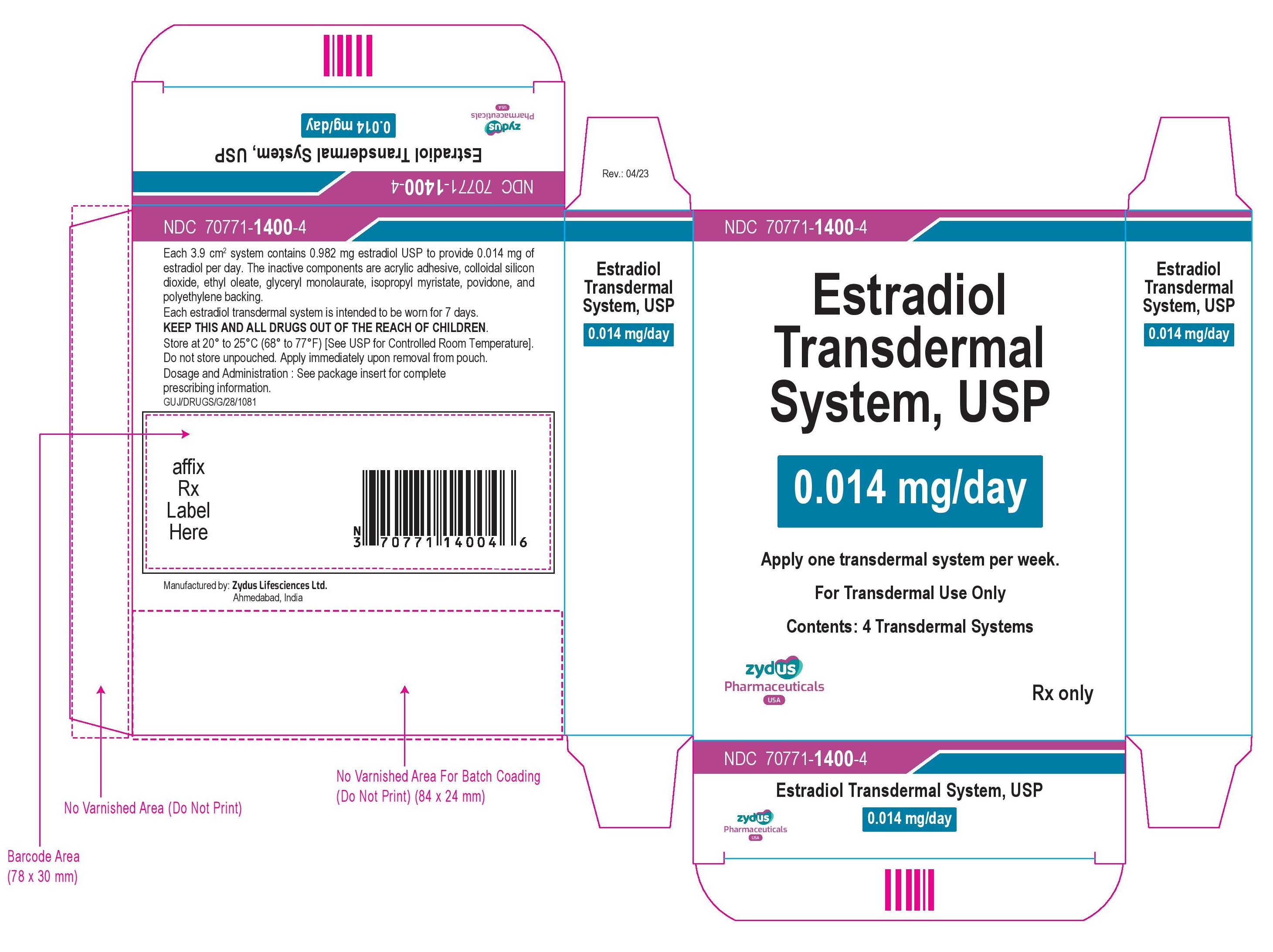 DRUG LABEL: estradiol
NDC: 70771-1400 | Form: PATCH
Manufacturer: Zydus Lifesciences Limited
Category: prescription | Type: HUMAN PRESCRIPTION DRUG LABEL
Date: 20230421

ACTIVE INGREDIENTS: ESTRADIOL 0.014 mg/1 d
INACTIVE INGREDIENTS: SILICON DIOXIDE; ETHYL OLEATE; ISOPROPYL MYRISTATE; GLYCERYL LAURATE; POVIDONE; 2-ETHYLHEXYL ACRYLATE; 2-HYDROXYETHYL ACRYLATE; GLYCIDYL METHACRYLATE

PACKAGE LABEL.PRINCIPAL DISPLAY PANEL

NDC 70771-1400-4

Estradiol Transdermal System, USP

0.014 mg/day

Apply one transdermal system per week.

For Transdermal Use Only

Contents: 4 Transdermal Systems

Rx Only

zydus Pharmaceuticals USA